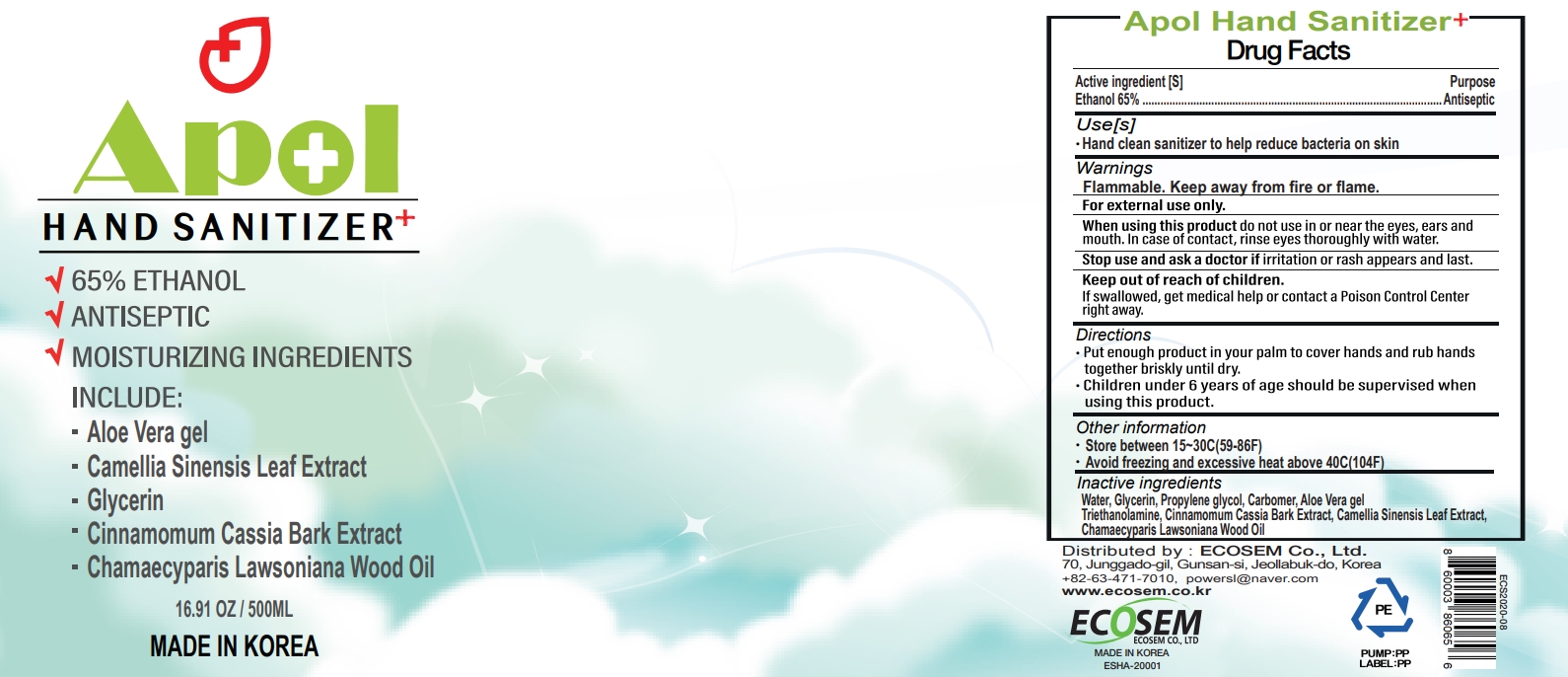 DRUG LABEL: APOL HAND SANITIZER
NDC: 80082-201 | Form: GEL
Manufacturer: ECOSEM CO., LTD
Category: otc | Type: HUMAN OTC DRUG LABEL
Date: 20200805

ACTIVE INGREDIENTS: ALCOHOL 65 mL/100 mL
INACTIVE INGREDIENTS: CHINESE CINNAMON; TROLAMINE; GREEN TEA LEAF; CHAMAECYPARIS LAWSONIANA WOOD OIL; WATER; GLYCERIN; PROPYLENE GLYCOL; CARBOMER HOMOPOLYMER, UNSPECIFIED TYPE; ALOE VERA LEAF

80082-201

Active ingredient

Ethanol 65%

Purpose

Antiseptic

Use

Hand clean sanitizer to help reduce bacteria on skin

Warnings

Flammable. Keep away from fire or flame.

For external use only.

When using this product

do not use in or near the eyes, ears and mouth. In case of contact, rinse eyes thoroughly with water.

Stop use and ask a doctor if

irritation or rash appears and last.

Keep out of reach of children.

If swallowed, get medical help or contact a Poison Control Center right away.

Directions

Put enough product in your palm to cover hands and rub hands together briskly until dry.

Children under 6 years of age should be supervised when using this product.

Other information

Store between 15-30C(59-86F)

Avoid freezing and excessive heat above 40C(104F)

Inactive ingredients

Water, Glycerin, Propylene glycol, Carbomer, Aloe Vera gel Triethanolamine, Cinnamomum Cassia Bark Extract, Camellia Sinensis Leaf Extract, Chamaecyparis Lawsoniana Wood Oil